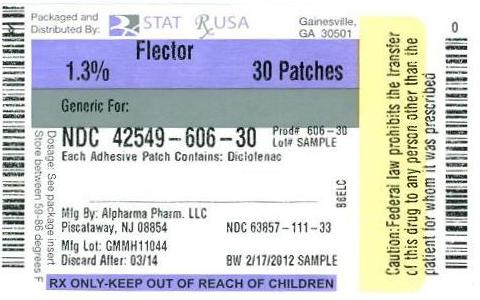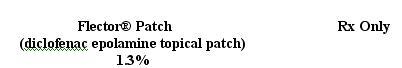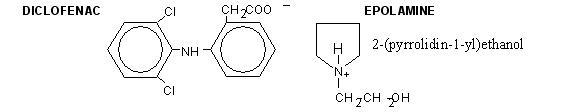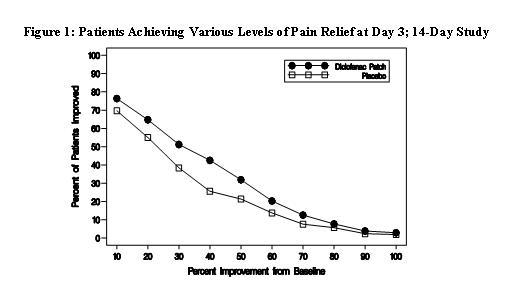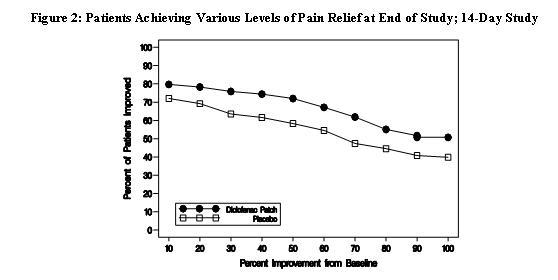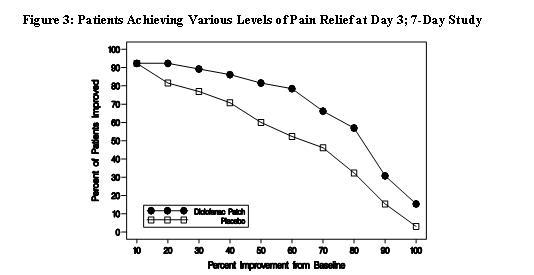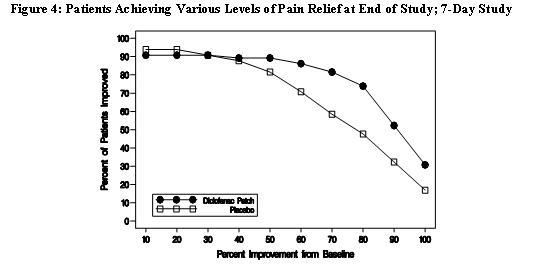 DRUG LABEL: Flector
NDC: 42549-606 | Form: PATCH
Manufacturer: STAT Rx USA LLC
Category: prescription | Type: HUMAN PRESCRIPTION DRUG LABEL
Date: 20120221

ACTIVE INGREDIENTS: DICLOFENAC EPOLAMINE 180 mg/1 1
INACTIVE INGREDIENTS: BUTYLENE GLYCOL; DIHYDROXYALUMINUM AMINOACETATE; EDETATE DISODIUM; GELATIN; KAOLIN; METHYLPARABEN; POLYSORBATE 80; POVIDONE; PROPYLENE GLYCOL; PROPYLPARABEN; CARBOXYMETHYLCELLULOSE SODIUM; TARTARIC ACID; TITANIUM DIOXIDE; WATER

Flector® Patch
(diclofenac epolamine topical patch) 1.3%

Cardiovascular Risk

- NSAIDs^1 may cause an increased risk of serious cardiovascular thrombotic events, myocardial infarction, and stroke, which can be fatal. This risk may increase with duration of use. Patients with cardiovascular disease or risk factors for cardiovascular disease may be at greater risk. (SeeWARNINGS andCLINICAL TRIALS).
- Flector® Patch is contraindicated for the treatment of peri-operative pain in the setting of coronary artery bypass graft (CABG) surgery (seeWARNINGS).

Gastrointestinal Risk

- NSAIDs cause an increased risk of serious gastrointestinal adverse events including bleeding, ulceration, and perforation of the stomach or intestines, which can be fatal. These events can occur at any time during use and without warning symptoms. Elderly patients are at greater risk for serious gastrointestinal events. (SeeWARNINGS).

^1 Throughout this package insert, the term NSAID refers to a non-aspirin non-steroidal anti-inflammatory drug.

DESCRIPTION

Flector® Patch (10 cm x 14 cm) is comprised of an adhesive material containing 1.3% diclofenac epolamine which is applied to a non-woven polyester felt backing and covered with a polypropylene film release liner. The release liner is removed prior to topical application to the skin.

Diclofenac epolamine is a non-opioid analgesic chemically designated as 2-[(2,6-dichlorophenyl) amino]benzeneacetic acid, (2-(pyrrolidin-1-yl) ethanol salt, with a molecular formula of C20H24Cl2N2O3 (molecular weight 411.3), an n-octanol/water partition coefficient of 8 at pH 8.5, and the following structure:

Each adhesive patch contains 180 mg of diclofenac epolamine (13 mg per gram adhesive) in an aqueous base. It also contains the following inactive ingredients: 1,3-butylene glycol, dihydroxyaluminum aminoacetate, disodium edetate, D-sorbitol, fragrance (Dalin PH), gelatin, kaolin, methylparaben, polysorbate 80, povidone, propylene glycol, propylparaben, sodium carboxymethylcellulose, sodium polyacrylate, tartaric acid, titanium dioxide, and purified water.

CLINICAL PHARMACOLOGY

Pharmacodynamics

Flector® Patch applied to intact skin provides local analgesia by releasing diclofenac epolamine from the patch into the skin. Diclofenac is a nonsteroidal anti-inflammatory drug (NSAID). In pharmacologic studies, diclofenac has shown anti-inflammatory, analgesic, and antipyretic activity. As with other NSAIDs, its mode of action is not known; its ability to inhibit prostaglandin synthesis, however, may be involved in its anti-inflammatory activity, as well as contribute to its efficacy in relieving pain associated with inflammation.

Pharmacokinetics

Absorption

Following a single application of the Flector Patch on the upper inner arm, peak plasma concentrations of diclofenac (range 0.7 – 6 ng/mL) were noted between 10 – 20 hours of application. Plasma concentrations of diclofenac in the range of 1.3 – 8.8 ng/mL were noted after five days with twice-a-day Flector Patch application.

Systemic exposure (AUC) and maximum plasma concentrations of diclofenac, after repeated dosing for four days with Flector® Patch, were lower (<1%) than after a single oral 50 mg diclofenac sodium tablet.

The pharmacokinetics of Flector® Patch has been tested in healthy volunteers at rest or undergoing moderate exercise (cycling 20 min/h for 12 h at a mean HR of 100.3 bpm). No clinically relevant differences in systemic absorption were observed, with peak plasma concentrations in the range of 2.2 – 8.1 ng/m while resting, and 2.7 – 7.2 ng/mL during exercise.

Distribution

Diclofenac has a very high affinity (>99%) for human serum albumin.

Metabolism and Excretion

The plasma elimination half-life of diclofenac after application of Flector Patch is approximately 12 hours. Diclofenac is eliminated through metabolism and subsequent urinary and biliary excretion of the glucuronide and the sulfate conjugates of the metabolites.

CLINICAL STUDIES

Efficacy of Flector® Patch was demonstrated in two of four studies of patients with minor sprains, strains, and contusions. Patients were randomly assigned to treatment with the Flector® Patch, or a placebo patch identical to the Flector® Patch minus the active ingredient. In the first of these two studies, patients with ankle sprains were treated once daily for a week. In the second study, patients with sprains, strains and contusions were treated twice daily for up to two weeks. Pain was assessed over the period of treatment. Patients treated with the Flector® Patch experienced a greater reduction in pain as compared to patients randomized to placebo patch as evidenced by the responder curves presented below.

INDICATIONS AND USAGE

Carefully consider the potential benefits and risks of Flector® Patch and other treatment options before deciding to use Flector® Patch. Use the lowest effective dose for the shortest duration consistent with individual patient treatment goals (seeWARNINGS).

Flector® Patch is indicated for the topical treatment of acute pain due to minor strains, sprains, and contusions.

CONTRAINDICATIONS

Flector® Patch is contraindicated in patients with known hypersensitivity to diclofenac.

Flector® Patch should not be given to patients who have experienced asthma, urticaria, or allergic-type reactions after taking aspirin or other NSAIDs. Severe, rarely fatal, anaphylactic-like reactions to NSAIDs have been reported in such patients (seeWARNINGS - Anaphylactoid Reactions, andPRECAUTIONS - Preexisting Asthma).

Flector® Patch is contraindicated for the treatment of peri-operative pain in the setting of coronary artery bypass graft (CABG) surgery (seeWARNINGS).

Flector® Patch should not be applied to non-intact or damaged skin resulting from any etiology e.g. exudative dermatitis, eczema, infected lesion, burns or wounds.

WARNINGS

CARDIOVASCULAR EFFECTS

Cardiovascular Thrombotic Events

Clinical trials of several COX-2 selective and nonselective NSAIDs of up to three years duration have shown an increased risk of serious cardiovascular (CV) thrombotic events, myocardial infarction, and stroke, which can be fatal. All NSAIDs, both COX-2 selective and nonselective, may have a similar risk. Patients with known CV disease or risk factors for CV disease may be at greater risk. To minimize the potential risk for an adverse CV event in patients treated with an NSAID, the lowest effective dose should be used for the shortest duration possible. Physicians and patients should remain alert for the development of such events, even in the absence of previous CV symptoms. Patients should be informed about the signs and/or symptoms of serious CV events and the steps to take if they occur.

There is no consistent evidence that concurrent use of aspirin mitigates the increased risk of serious CV thrombotic events associated with NSAID use. The concurrent use of aspirin and an NSAID does increase the risk of serious GI events (seeGI WARNINGS).

Two large, controlled, clinical trials of a COX-2 selective NSAID for the treatment of pain in the first 10-14 days following CABG surgery found an increased incidence of myocardial infarction and stroke (seeCONTRAINDICATIONS).

Hypertension

NSAIDs, including Flector® Patch, can lead to onset of new hypertension or worsening of pre-existing hypertension, either of which may contribute to the increased incidence of CV events. Patients taking thiazides or loop diuretics may have impaired response to these therapies when taking NSAIDs. NSAIDs, including Flector® Patch, should be used with caution in patients with hypertension. Blood pressure (BP) should be monitored closely during the initiation of NSAID treatment and throughout the course of therapy.

Congestive Heart Failure and Edema

Fluid retention and edema have been observed in some patients taking NSAIDs. Flector® Patch should be used with caution in patients with fluid retention or heart failure.

Gastrointestinal Effects- Risk of Ulceration, Bleeding, and Perforation

NSAIDs, including Flector® Patch, can cause serious gastrointestinal (GI) adverse events including inflammation, bleeding, ulceration, and perforation of the stomach, small intestine, or large intestine, which can be fatal. These serious adverse events can occur at any time, with or without warning symptoms, in patients treated with NSAIDs. Only one in five patients, who develop a serious upper GI adverse event on NSAID therapy, is symptomatic. Upper GI ulcers, gross bleeding, or perforation caused by NSAIDs occur in approximately 1% of patients treated for 3-6 months, and in about 2-4% of patients treated for one year. These trends continue with longer duration of use, increasing the likelihood of developing a serious GI event at some time during the course of therapy. However, even short-term therapy is not without risk.

NSAIDs should be prescribed with extreme caution in those with a prior history of ulcer disease or gastrointestinal bleeding. Patients with a prior history of peptic ulcer disease and/or gastrointestinal bleeding who use NSAIDs have a greater than 10-fold increased risk for developing a GI bleed compared to patients with neither of these risk factors. Other factors that increase the risk for GI bleeding in patients treated with NSAIDs include concomitant use of oral corticosteroids or anticoagulants, longer duration of NSAID therapy, smoking, use of alcohol, older age, and poor general health status. Most spontaneous reports of fatal GI events are in elderly or debilitated patients and therefore, special care should be taken in treating this population.

To minimize the potential risk for an adverse GI event in patients treated with an NSAID, the lowest effective dose should be used for the shortest possible duration. Patients and physicians should remain alert for signs and symptoms of GI ulceration and bleeding during NSAID therapy and promptly initiate additional evaluation and treatment if a serious GI adverse event is suspected. This should include discontinuation of the NSAID until a serious GI adverse event is ruled out. For high risk patients, alternate therapies that do not involve NSAIDs should be considered.

Renal Effects

Long-term administration of NSAIDs has resulted in renal papillary necrosis and other renal injury. Renal toxicity has also been seen in patients in whom renal prostaglandins have a compensatory role in the maintenance of renal perfusion. In these patients, administration of a nonsteroidal anti-inflammatory drug may cause a dose-dependent reduction in prostaglandin formation and, secondarily, in renal blood flow, which may precipitate overt renal decompensation. Patients at greatest risk of this reaction are those with impaired renal function, heart failure, liver dysfunction, those taking diuretics and ACE inhibitors, and the elderly. Discontinuation of NSAID therapy is usually followed by recovery to the pretreatment state.

Advanced Renal Disease

No information is available from controlled clinical studies regarding the use of Flector® Patch in patients with advanced renal disease. Therefore, treatment with Flector® Patch is not recommended in these patients with advanced renal disease. If Flector® Patch therapy is initiated, close monitoring of the patient's renal function is advisable.

Anaphylactoid Reactions

As with other NSAIDs, anaphylactoid reactions may occur in patients without known prior exposure to Flector® Patch. Flector® Patch should not be given to patients with the aspirin triad. This symptom complex typically occurs in asthmatic patients who experience rhinitis with or without nasal polyps, or who exhibit severe, potentially fatal bronchospasm after taking aspirin or other NSAIDs (seeCONTRAINDICATIONS andPRECAUTIONS - Preexisting Asthma). Emergency help should be sought in cases where an anaphylactoid reaction occurs.

Skin Reactions

NSAIDs, including Flector® Patch, can cause serious skin adverse events such as exfoliative dermatitis, Stevens-Johnson Syndrome (SJS), and toxic epidermal necrolysis (TEN), which can be fatal. These serious events may occur without warning. Patients should be informed about the signs and symptoms of serious skin manifestations and use of the drug should be discontinued at the first appearance of skin rash or any other sign of hypersensitivity.

Pregnancy

In late pregnancy, as with other NSAIDs, Flector® Patch should be avoided because it may cause premature closure of the ductus arteriosus.

PRECAUTIONS

General

Flector® Patch cannot be expected to substitute for corticosteroids or to treat corticosteroid insufficiency. Abrupt discontinuation of corticosteroids may lead to disease exacerbation. Patients on prolonged corticosteroid therapy should have their therapy tapered slowly if a decision is made to discontinue corticosteroids.

The pharmacological activity of Flector® Patch in reducing inflammation may diminish the utility of these diagnostic signs in detecting complications of presumed noninfectious, painful conditions.

Hepatic Effects

Borderline elevations of one or more liver tests may occur in up to 15% of patients taking NSAIDs including Flector® Patch. These laboratory abnormalities may progress, may remain unchanged, or may be transient with continuing therapy. Notable elevations of ALT or AST (approximately three or more times the upper limit of normal) have been reported in approximately 1% of patients in clinical trials with NSAIDs. In addition, rare cases of severe hepatic reactions, including jaundice and fatal fulminant hepatitis, liver necrosis and hepatic failure, some of them with fatal outcomes have been reported.

A patient with symptoms and/or signs suggesting liver dysfunction, or in whom an abnormal liver test has occurred, should be evaluated for evidence of the development of a more severe hepatic reaction while on therapy with Flector® Patch. If clinical signs and symptoms consistent with liver disease develop, or if systemic manifestations occur (e.g., eosinophilia, rash, etc.), Flector® Patch should be discontinued.

Hematological Effects

Anemia is sometimes seen in patients receiving NSAIDs. This may be due to fluid retention, occult or gross GI blood loss, or an incompletely described effect upon erythropoiesis. Patients on long-term treatment with NSAIDs, including Flector® Patch, should have their hemoglobin or hematocrit checked if they exhibit any signs or symptoms of anemia.

NSAIDs inhibit platelet aggregation and have been shown to prolong bleeding time in some patients. Unlike aspirin, their effect on platelet function is quantitatively less, of shorter duration, and reversible. Patients receiving Flector® Patch who may be adversely affected by alterations in platelet function, such as those with coagulation disorders or patients receiving anticoagulants, should be carefully monitored.

Preexisting Asthma

Patients with asthma may have aspirin-sensitive asthma. The use of aspirin in patients with aspirin-sensitive asthma has been associated with severe bronchospasm which can be fatal. Since cross reactivity, including bronchospasm, between aspirin and other nonsteroidal anti-inflammatory drugs has been reported in such aspirin-sensitive patients, Flector® Patch should not be administered to patients with this form of aspirin sensitivity and should be used with caution in patients with preexisting asthma.

Eye Exposure

Contact of Flector® Patch with eyes and mucosa, although not studied, should be avoided. If eye contact occurs, immediately wash out the eye with water or saline. Consult a physician if irritation persists for more than an hour.

Accidental Exposure in Children

Even a used Flector® Patch contains a large amount of diclofenac epolamine (as much as 170 mg). The potential therefore exists for a small child or pet to suffer serious adverse effects from chewing or ingesting a new or used Flector® Patch. It is important for patients to store and dispose of Flector® Patch out of the reach of children and pets.

Information for Patients

Patients should be informed of the following information before initiating therapy with an NSAID and periodically during the course of ongoing therapy. Patients should also be encouraged to read the NSAID Medication Guide that accompanies each prescription dispensed.

1. Flector® Patch, like other NSAIDs, may cause serious CV side effects, such as MI or stroke, which may result in hospitalization and even death. Although serious CV events can occur without warning symptoms, patients should be alert for the signs and symptoms of chest pain, shortness of breath, weakness, slurring of speech, and should ask for medical advice when observing any indicative sign or symptoms. Patients should be apprised of the importance of this follow-up (seeWARNINGS, Cardiovascular Effects).
2. Flector® Patch, like other NSAIDs, may cause GI discomfort and, rarely, serious GI side effects, such as ulcers and bleeding, which may result in hospitalization and even death. Although serious GI tract ulcerations and bleeding can occur without warning symptoms, patients should be alert for the signs and symptoms of ulcerations and bleeding, and should ask for medical advice when observing any indicative sign or symptoms including epigastric pain, dyspepsia, melena, and hematemesis. Patients should be apprised of the importance of this follow-up (seeWARNINGS, Gastrointestinal Effects: Risk of Ulceration, Bleeding, and Perforation).
3. Flector® Patch, like other NSAIDs, may cause serious skin side effects such as exfoliative dermatitis, SJS, and TEN, which may result in hospitalizations and even death. Although serious skin reactions may occur without warning, patients should be alert for the signs and symptoms of skin rash and blisters, fever, or other signs of hypersensitivity such as itching, and should ask for medical advice when observing any indicative signs or symptoms. Patients should be advised to stop the drug immediately if they develop any type of rash and contact their physicians as soon as possible.
4. Patients should be instructed to promptly report signs or symptoms of unexplained weight gain or edema to their physicians (seeWARNINGS, Cardiovascular Effects).
5. Patients should be informed of the warning signs and symptoms of hepatotoxicity (e.g., nausea, fatigue, lethargy, pruritus, jaundice, right upper quadrant tenderness, and "flu-like" symptoms). If these occur, patients should be instructed to stop therapy and seek immediate medical therapy.
6. Patients should be informed of the signs of an anaphylactoid reaction (e.g. difficulty breathing, swelling of the face or throat). If these occur, patients should be instructed to seek immediate emergency help (seeWARNINGS).
7. In late pregnancy, as with other NSAIDs, Flector® Patch should be avoided because it may cause premature closure of the ductus arteriosus.
8. Patients should be advised not to use Flector® Patch if they have a aspirin-sensitive asthma. Flector® Patch, like other NSAIDs, could cause severe and even fatal bronchospasm in these patients (seePRECAUTIONS, Preexisting asthma). Patients should discontinue use of Flector® Patch and should immediately seek emergency help if they experience wheezing or shortness of breath.
9. Patients should be informed that Flector® Patch should be used only on intact skin.
10. Patients should be advised to avoid contact of Flector® Patch with eyes and mucosa. Patients should be instructed that if eye contact occurs, they should immediately wash out the eye with water or saline, and consult a physician if irritation persists for more than an hour.
11. Patients and caregivers should be instructed to wash their hands after applying, handling or removing the patch.
12. Patients should be informed that, if Flector® Patch begins to peel off, the edges of the patch may be taped down.
13. Patients should be instructed not to wear Flector® Patch during bathing or showering. Bathing should take place in between scheduled patch removal and application (seeDOSAGE AND ADMINISTRATION).
14. Patients should be advised to store Flector® Patch and to discard used patches out of the reach of children and pets. If a child or pet accidentally ingests Flector® Patch, medical help should be sought immediately (seePRECAUTIONS, Accidental Exposure in Children).

Laboratory Tests

Because serious GI tract ulcerations and bleeding can occur without warning symptoms, physicians should monitor for signs or symptoms of GI bleeding. Patients on long-term treatment with NSAIDs, should have their CBC and a chemistry profile checked periodically. If clinical signs and symptoms consistent with liver or renal disease develop, systemic manifestations occur (e.g., eosinophilia, rash, etc.) or if abnormal liver tests persist or worsen, Flector® Patch should be discontinued.

Drug Interactions

ACE-inhibitors

Reports suggest that NSAIDs may diminish the antihypertensive effect of ACE-inhibitors. This interaction should be given consideration in patients taking NSAIDs concomitantly with ACE-inhibitors.

Aspirin

When Flector® Patch is administered with aspirin, the binding of diclofenac to protein is reduced, although the clearance of free diclofenac is not altered. The clinical significance of this interaction is not known; however, as with other NSAIDs, concomitant administration of diclofenac and aspirin is not generally recommended because of the potential of increased adverse effects.

Diuretics

Clinical studies, as well as post marketing observations, have shown that Flector® Patch may reduce the natriuretic effect-of furosemide and thiazides in some patients. This response has been attributed to inhibition of renal prostaglandin synthesis. During concomitant therapy with NSAIDs, the patient should be observed closely for signs of renal failure (seeWARNINGS, Renal Effects), as well as to assure diuretic efficacy.

Lithium

NSAIDs have produced an elevation of plasma lithium levels and a reduction in renal lithium clearance. The mean minimum lithium concentration increased 15% and the renal clearance was decreased by approximately 20%. These effects have been attributed to inhibition of renal prostaglandin synthesis by the NSAID. Thus, when NSAIDs and lithium are administered concurrently, subjects should be observed carefully for signs of lithium toxicity.

Methotrexate

NSAIDs have been reported to competitively inhibit methotrexate accumulation in rabbit kidney slices. This may indicate that they could enhance the toxicity of methotrexate. Caution should be used when NSAIDs are administered concomitantly with methotrexate.

Warfarin

The effects of warfarin and NSAIDs on GI bleeding are synergistic, such that users of both drugs together have a risk of serious GI bleeding higher than users of either drug alone.

Carcinogenesis, Mutagenesis, Impairment of Fertility

Carcinogenesis

Long-term studies in animals have not been performed to evaluate the carcinogenic potential of either diclofenac epolamine or Flector Patch.

Mutagenesis

Diclofenac epolamine is not mutagenic in Salmonella Typhimurium strains, nor does it induce an increase in metabolic aberrations in cultured human lymphocytes, or the frequency of micronucleated cells in the bone marrow micronucleus test performed in rats.

Impairment of Fertility

Male and female Sprague Dawley rats were administered 1, 3, or 6 mg/kg/day diclofenac epolamine via oral gavage (males treated for 60 days prior to conception and during mating period, females treated for 14 days prior to mating through day 19 of gestation). Diclofenac epolamine treatment with 6 mg/kg/day resulted in increased early resorptions and postimplantation losses; however, no effects on the mating and fertility indices were found. The 6 mg/kg/day dose corresponds to 3-times the maximum recommended daily exposure in humans based on a body surface area comparison.

Pregnancy

Teratogenic Effects Pregnancy Category C.

Pregnant Sprague Dawley rats were administered 1, 3, or 6 mg/kg diclofenac epolamine via oral gavage daily from gestation days 6-15. Maternal toxicity, embryotoxicity, and increased incidence of skeletal anomalies were noted with 6 mg/kg/day diclofenac epolamine, which corresponds to 3-times the maximum recommended daily exposure in humans based on a body surface area comparison. Pregnant New Zealand White rabbits were administered 1, 3, or 6 mg/kg diclofenac epolamine vial oral gavage daily from gestation days 6-18. No maternal toxicity was noted; however, embryotoxicity was evident at 6 mg/kg/day group which corresponds to 6.5-times the maximum recommended daily exposure in humans based on a body surface area comparison.

There are no adequate and well-controlled studies in pregnant women. Flector Patch should be used during pregnancy only if the potential benefit justifies the potential risk to the fetus.

Nonteratogenic Effects

Because of the known effects of nonsteroidal anti-inflammatory drugs on the fetal cardiovascular system (closure of ductus arteriosus), use during pregnancy (particularly late pregnancy) should be avoided.

Male rats were orally administered diclofenac epolamine (1, 3, 6 mg/kg) for 60 days prior to mating and throughout the mating period, and females were given the same doses 14 days prior to mating and through mating, gestation, and lactation. Embryotoxicity was observed at 6 mg/kg diclofenac epolamine (3-times the maximum recommended daily exposure in humans based on a body surface area comparison), and was manifested as an increase in early resorptions, post-implantation losses, and a decrease in live fetuses. The number of live born and total born were also reduced as was F1 postnatal survival, but the physical and behavioral development of surviving F1 pups in all groups was the same as the deionized water control, nor was reproductive performance adversely affected despite a slight treatment-related reduction in body weight.

Labor and Delivery

In rat studies with NSAIDs, as with other drugs known to inhibit prostaglandin synthesis, an increased incidence of dystocia, delayed parturition, and decreased pup survival occurred. The effects of Flector® Patch on labor and delivery in pregnant women are unknown.

Nursing Mothers

It is not known whether this drug is excreted in human milk. Because many drugs are excreted in human-milk and because of the potential for serious adverse reactions in nursing infants from Flector® Patch, a decision should be made whether to discontinue nursing or to discontinue the drug, taking into account the importance of the drug to the mother.

Pediatric Use

Safety and effectiveness in pediatric patients have not been established.

Geriatric Use

Clinical studies of Flector® Patch did not include sufficient numbers of subjects aged 65 and over to determine whether they respond differently from younger subjects. Other reported clinical experience has not identified differences in responses between the elderly and younger patients.

Diclofenac, as with any NSAID, is known to be substantially excreted by the kidney, and the risk of toxic reactions to Flector® Patch may be greater in patients with impaired renal function. Because elderly patients are more likely to have decreased renal function, care should be taken when using Flector® Patch in the elderly, and it may be useful to monitor renal function.

ADVERSE REACTIONS

In controlled trials during the premarketing development of Flector® Patch, approximately 600 patients with minor sprains, strains, and contusions have been treated with Flector® Patch for up to two weeks.

Adverse Events Leading to Discontinuation of Treatment

In the controlled trials, 3% of patients in both the Flector® Patch and placebo patch groups discontinued treatment due to an adverse event. The most common adverse events leading to discontinuation were application site reactions, occurring in 2% of both the Flector® Patch and placebo patch groups. Application site reactions leading to dropout included pruritus, dermatitis, and burning.

Common Adverse Events

Localized Reactions

Overall, the most common adverse events associated with Flector® Patch treatment were skin reactions at the site of treatment.

Table 1 lists all adverse events, regardless of causality, occurring in ≥ 1% of patients in controlled trials of Flector® Patch. A majority of patients treated with Flector® Patch had adverse events with a maximum intensity of “mild” or “moderate.”

Table 1. Common Adverse Events (by body system and preferred term) in ≥1% of Patients treated with Flector® Patch or Placebo Patch^1
 | Diclofenac N=572 |  | Placebo N=564
 | N | Percent | N | Percent
Application Site Conditions | 64 | 11 | 70 | 12
Pruritus | 31 | 5 | 44 | 8
Dermatitis | 9 | 2 | 3 | < 1
Burning | 2 | <1 | 8 | 1
Other^2 | 22 | 4 | 15 | 3
Gastrointestinal Disorders | 49 | 9 | 33 | 6
Nausea | 17 | 3 | 11 | 2
Dysgeusia | 10 | 2 | 3 | < 1
Dyspepsia | 7 | 1 | 8 | 1
Other^3 | 15 | 3 | 11 | 2
Nervous System Disorders | 13 | 2 | 18 | 3
Headache | 7 | 1 | 10 | 2
Paresthesia | 6 | 1 | 8 | 1
Somnolence | 4 | 1 | 6 | 1
Other^4 | 4 | 1 | 3 | < 1
^1 The table lists adverse events occurring in placebo-treated patients because the placebo-patch was comprised of the same ingredients as Flector® Patch except for diclofenac. Adverse events in the placebo group may therefore reflect effects of the non-active ingredients.
^2 Includes: application site dryness, irritation, erythema, atrophy, discoloration, hyperhidriosis, and vesicles.
^3 Includes: gastritis, vomiting, diarrhea, constipation, upper abdominal pain, and dry mouth.
^4 Includes: hypoaesthesia, dizziness, and hyperkinesias.

Foreign labeling describes that dermal allergic reactions may occur with Flector® Patch treatment. Additionally, the treated area may become irritated or develop itching, erythema, edema, vesicles, or abnormal sensation.

DRUG ABUSE AND DEPENDENCE

Controlled Substance Class

Flector® Patch is not a controlled substance.

Physical and Psychological Dependence

Diclofenac, the active ingredient in Flector® Patch, is an NSAID that does not lead to physical or psychological dependence.

OVERDOSAGE

There is limited experience with overdose of Flector® Patch. In clinical studies, the maximum single dose administered was one Flector® Patch containing 180 mg of diclofenac epolamine. There were no serious adverse events.

Should systemic side effects occur due to incorrect use or accidental overdose of this product, the general measures recommended for intoxication with non-steroidal anti-inflammatory drugs should be taken.

DOSAGE AND ADMINISTRATION

Carefully consider the potential benefits and risks of Flector® Patch and other treatment options before deciding to use Flector® Patch. Use the lowest effective dose for the shortest duration consistent with individual patient treatment goals (seeWARNINGS).

The recommended dose of Flector® Patch is one (1) patch to the most painful area twice a day.

Flector® patch should not be applied to damaged or non-intact skin.

Flector® patch should not be worn when bathing or showering.

HANDLING AND DISPOSAL

Patients and caregivers should wash their hands after applying, handling or removing the patch. Eye contact should be avoided.

HOW SUPPLIED

The Flector® Patch is supplied in resealable envelopes, each containing 5 patches (NDC 42549-606-05) (10 cm x 14 cm), with 6 envelopes per box (NDC 42549-606-30). Each individual patch is embossed with “Diclofenac Epolamine Patch 1.3%”.

- Each patch contains 180 mg of diclofenac epolamine in an aqueous base (13 mg of active per gram of adhesive or 1.3%).
- The product is intended for topical use only
- Keep out of reach of children and pets.
- The ENVELOPES SHOULD BE SEALED AT ALL TIMES WHEN NOT IN USE.
- Store at 25ºC (77ºF); excursions permitted to 15º-30ºC (59º-86ºF). [See USP Controlled Room Temperature].

Manufacturer: Teikoku Seiyaku Co., Ltd., Sanbonmatsu, Kagawa 769-2695, Japan
Distributor: Alpharma Pharmaceuticals LLC, One New England Avenue, Piscataway, NJ 08854 (Telephone: 1-877-452-3426)

Version June 2008
8283
Ed II/06.08

Relabeling and Repackaging by:
STAT Rx USA LLC
Gainesville, GA 30501

Medication Guide for Non-Steroidal Anti-Inflammatory Drugs (NSAIDs)

(See the end of this Medication Guide for a list of prescription NSAID medicines.)

What is the most important information I should know about medicines called Non-Steroidal Anti-Inflammatory Drugs (NSAIDs)?

NSAID medicines may increase the chance of a heart attack or stroke that can lead to death. This chance increases:
● with longer use of NSAID medicines
● in people who have heart disease

NSAID medicines should never be used right before or after a heart surgery called a “coronary artery bypass graft (CABG).”

NSAID medicines can cause ulcers and bleeding in the stomach and intestines at any time during treatment. Ulcers and bleeding:● can happen without warning symptoms
● may cause death

The chance of a person getting an ulcer or bleeding increases with:● taking medicines called “corticosteroids” and “anticoagulants”
● longer use
● smoking
● drinking alcohol
● older age
● having poor health

NSAID medicines should only be used:● exactly as prescribed
● at the lowest dose possible for your treatment
● for the shortest time needed

What are Non-Steroidal Anti-Inflammatory Drugs (NSAIDs)?

NSAID medicines are used to treat pain and redness, swelling, and heat (inflammation) from medical conditions such as:

- different types of arthritis
- menstrual cramps and other types of short-term pain

Who should not take a Non-Steroidal Anti-Inflammatory Drug (NSAID)?

Do not take an NSAID medicine:

- if you had an asthma attack, hives, or other allergic reaction with aspirin or any other NSAID medicine
- for pain right before or after heart bypass surgery

Tell your healthcare provider:

- about all your medical conditions.
- about all of the medicines you take. NSAIDs and some other medicines can interact with each other and cause serious side effects. Keep a list of your medicines to show to your healthcare provider and pharmacist.
- if you are pregnant. NSAID medicines should not be used by pregnant women late in their pregnancy.
- if you are breastfeeding. Talk to your doctor.

What are the possible side effects of Non-Steroidal Anti-Inflammatory Drugs (NSAIDs)?

Serious side effects include: | Other side effects include:
● heart attack | ● stomach pain
● stroke | ● constipation
● high blood pressure | ● diarrhea
● heart failure from body swelling (fluid retention) | ● gas
● kidney problems including kidney failure | ● heartburn
● bleeding and ulcers in the stomach and intestine | ● nausea
● low red blood cells (anemia) | ● vomiting
● life-threatening skin reactions | ● dizziness
● life-threatening allergic reactions
● liver problems including liver failure
● asthma attacks in people who have asthma

Get emergency help right away if you have any of the following symptoms:

- shortness of breath or trouble breathing
- chest pain
- weakness in one part or side of your body
- slurred speech
- swelling of the face or throat

Stop your NSAID medicine and call your healthcare provider right away if you have any of the following symptoms:

- nausea
- more tired or weaker than usual
- itching
- your skin or eyes look yellow
- stomach pain
- flu-like symptoms
- vomit blood
- there is blood in your bowel movement or it is black and sticky like tar
- unusual weight gain
- skin rash or blisters with fever
- swelling of the arms and legs, hands and feet

These are not all the side effects with NSAID medicines. Talk to your healthcare provider or pharmacist for more information about NSAID medicines.

Other information about Non-Steroidal Anti-Inflammatory Drugs (NSAIDs)

- Aspirin is an NSAID medicine but it does not increase the chance of a heart attack. Aspirin can cause bleeding in the brain, stomach, and intestines. Aspirin can also cause ulcers in the stomach and intestines.
- Some of these NSAID medicines are sold in lower doses without a prescription (over-the-counter). Talk to your healthcare provider before using over-the-counter NSAIDs for more than 10 days.

NSAID medicines that need a prescription

Generic Name | Tradename
Celecoxib | Celebrex
Diclofenac | Flector, Cataflam, Voltaren, Arthrotec (combined with misoprostol)
Diflunisal | Dolobid
Etodolac | Lodine, Lodine XL
Fenoprofen | Nalfon, Nalfon 200
Flurbirofen | Ansaid
Ibuprofen | Motrin, Tab-Profen, Vicoprofen (combined with hydrocodone), Combunox (combined with oxycodone)
Indomethacin | Indocin, Indocin SR, Indo-Lemmon, Indomethagan
Ketoprofen | Oruvail
Ketorolac | Toradol
Mefenamic Acid | Ponstel
Meloxicam | Mobic
Nabumetone | Relafen
Naproxen | Naprosyn, Anaprox, Anaprox DS, EC-Naproxyn, Naprelan, Naprapac (copackaged with lansoprazole)
Oxaprozin | Daypro
Piroxicam | Feldene
Sulindac | Clinoril
Tolmetin | Tolectin, Tolectin DS, Tolectin 600

This Medication Guide has been approved by the U.S. Food and Drug Administration.

Distributed by: Alpharma Pharmaceuticals LLC
One New England Avenue, Piscataway, NJ 08854 USA
(Telephone:1-888-840-8884) • www.FlectorPatch.com
Manufactured for: IBSA Institut Biochimique SA, CH-6903 Lugano, Switzerland
Manufactured by: Teikoku Seiyaku Co., Ltd., Sanbonmatsu, Kagawa 769-2695 Japan

Version June 2008
8283
Ed II/06.08

PRINCIPAL DISPLAY PANEL

NDC 42549-606-30
Flector Patch 1.3% #30 patch(s)
RX only